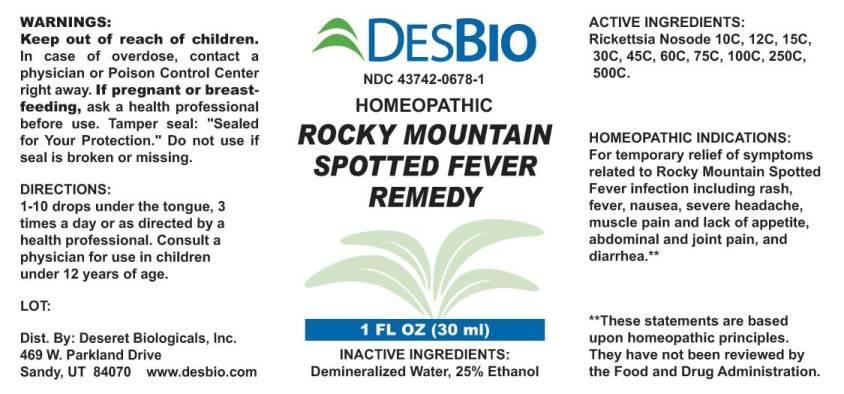 DRUG LABEL: Rocky Mountain Spotted Fever Remedy
NDC: 43742-0678 | Form: LIQUID
Manufacturer: Deseret Biologicals, Inc.
Category: homeopathic | Type: HUMAN OTC DRUG LABEL
Date: 20170412

ACTIVE INGREDIENTS: RICKETTSIA RICKETTSII 10 [hp_C]/1 mL
INACTIVE INGREDIENTS: WATER; ALCOHOL

DRUG FACTS:

ACTIVE INGREDIENT:

Rickettsia Nosode 10C, 12C, 15C, 30C, 45C, 60C, 75C, 100C, 250C, 500C.

HOMEOPATHIC INDICATIONS:

For temporary relief of symptoms related to Rocky Mountain Spotted Fever infection including rash, fever, nausea, severe headache, muscle pain and lack of appetite, abdominal and joint pain, and diarrhea.**

**These statements are based upon homeopathic principles. They have not been reviewed by the Food and Drug Administration.

WARNINGS:

Keep out of reach of children. In case of overdose, contact physician or Poison Control Center right away.

If pregnant or breast-feeding, ask a health professional before use.

Tamper seal: “Sealed for your protection.” Do not use if seal is broken or missing.

Keep out of reach of children. In case of overdose, contact physician or Poison Control Center right away.

DIRECTIONS:

1-10 drops under the tongue, 3 times a day or as directed by a health professional. Consult a physician for use in children under 12 years of age.

HOMEOPATHIC INDICATIONS:

For temporary relief of symptoms related to Rocky Mountain Spotted Fever infection including rash, fever, nausea, severe headache, muscle pain and lack of appetite, abdominal and joint pain, and diarrhea.**

**These statements are based upon homeopathic principles. They have not been reviewed by the Food and Drug Administration.

INACTIVE INGREDIENTS:

Demineralized Water, 25% Ethanol.

QUESTIONS:

Dist. By: Desert Biologicals, Inc.

469 W. Parkland Dr.

Sandy, UT 84070 www.desbio.com

PACKAGE LABEL DISPLAY:

DESBIO

NDC 43742-0678-1

HOMEOPATHIC

ROCKY MOUNTAIN

SPOTTED FEVER

REMEDY

1 FL OZ (30 ml)